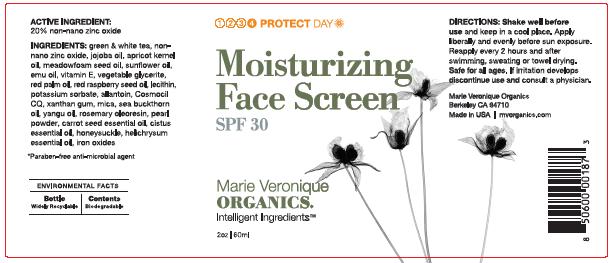 DRUG LABEL: Moisturizing Face Screen SPF 30
NDC: 62742-4056 | Form: CREAM
Manufacturer: Allure Labs, Inc.
Category: otc | Type: HUMAN OTC DRUG LABEL
Date: 20171221

ACTIVE INGREDIENTS: ZINC OXIDE 200 mg/1 mL
INACTIVE INGREDIENTS: JOJOBA OIL

Drug Facts

ACTIVE INGREDIENT:

20% non-nano zinc oxide

INACTIVE INGREDIENTS:

green and white tea, jojoba oil, apricot kernel oil, meadowfoam seed oil, sunflower oil, emu oil, vitamin E, vegetable glycerite, red palm oil, red raspberry seed oil, lecithin, potassium sorbate, allantoin, Cosmocil CQ, xanthan gum, mica, sea buckthorn oil, yangu oil, rosemary oleoresin, pearl powder, carrot seed essential oil, cistus essential oil, honeysuckle, helichrysum essential oil, iron oxides.

Cosmocil CQ is a paraben-free anti-microbial agent.

DIRECTIONS:

Shake well before use and keep in a cool place.

Apply liberally and evenly before sun exposure. Reapply every 2 hours and after swimming, sweating or towel drying.

Safe for all ages.

If irritation develops discontinue use and consult a physician.

OTHER INFORMATION:

ENVIRONMENTAL FACTS

Bottle widely Recyclable I Contents Biodegradable

DISTRIBUTOR:

Marie Veronique Organics
Berkeley CA 94710
Made in USA
mvorganics.com

PACKAGE LABEL

Moisturizing Face Screen

SPF 30

Marie Veronique ORGANICS.
Intelligent Ingredients

2oz / 60ml